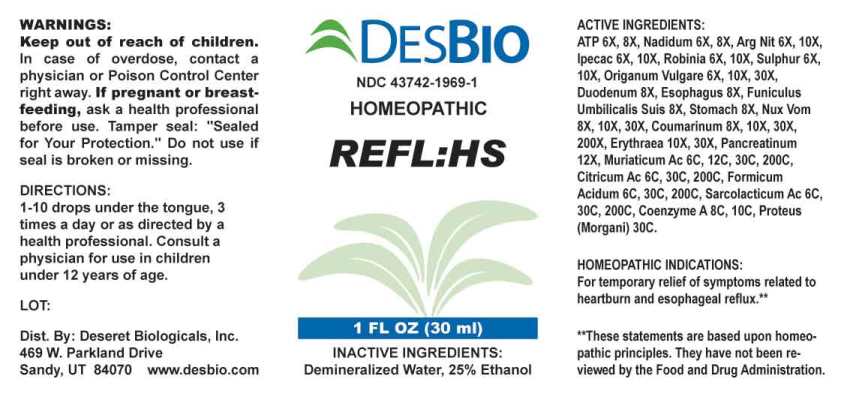 DRUG LABEL: REFL HS
NDC: 43742-1969 | Form: LIQUID
Manufacturer: Deseret Biologicals, Inc.
Category: homeopathic | Type: HUMAN OTC DRUG LABEL
Date: 20230717

ACTIVE INGREDIENTS: ADENOSINE TRIPHOSPHATE DISODIUM 6 [hp_X]/1 mL; NADIDE 6 [hp_X]/1 mL; SILVER NITRATE 6 [hp_X]/1 mL; IPECAC 6 [hp_X]/1 mL; ROBINIA PSEUDOACACIA BARK 6 [hp_X]/1 mL; SULFUR 6 [hp_X]/1 mL; OREGANO 6 [hp_X]/1 mL; SUS SCROFA DUODENUM 8 [hp_X]/1 mL; SUS SCROFA ESOPHAGUS 8 [hp_Q]/1 mL; SUS SCROFA UMBILICAL CORD 8 [hp_X]/1 mL; SUS SCROFA STOMACH 8 [hp_X]/1 mL; STRYCHNOS NUX-VOMICA SEED 8 [hp_X]/1 mL; COUMARIN 8 [hp_X]/1 mL; CENTAURIUM ERYTHRAEA 10 [hp_X]/1 mL; PANCRELIPASE 12 [hp_X]/1 mL; HYDROCHLORIC ACID 6 [hp_C]/1 mL; ANHYDROUS CITRIC ACID 6 [hp_C]/1 mL; FORMIC ACID 6 [hp_C]/1 mL; LACTIC ACID, L- 6 [hp_C]/1 mL; COENZYME A 8 [hp_C]/1 mL; PROTEUS MORGANII 30 [hp_C]/1 mL
INACTIVE INGREDIENTS: WATER; ALCOHOL

DRUG FACTS:

ACTIVE INGREDIENTS:

Adenosinum Triphosphoricum Dinatrum 6X, 8X, Nadidum 6X, 8X, Argentum Nitricum 6X, 10X, Ipecacuanha 6X, 10X, Robinia Pseudoacacia 6X, 10X, Sulphur 6X, 10X, Origanum Vulgare 6X, 10X, 30X, Duodenum (Suis) 8X, Esophagus (Suis) 8X, Funiculus Umbilicalis Suis 8X, Stomach (Suis) 8X, Nux Vomica 8X, 10X, 30X, Coumarinum 8X, 10X, 30X, 200X, Erythraea Centaurium 10X, 30X, Pancreatinum 12X, Muriaticum Acidum 6C, 12C, 30C, 200C, Citricum Acidum 6C, 30C, 200C, Formicum Acidum 6C, 30C, 200C, Sarcolacticum Acidum 6C, 30C, 200C, Coenzyme A 8C, 10C, Proteus (Morgani) 30C.

HOMEOPATHIC INDICATIONS:

For temporary relief of symptoms related to heartburn and esophageal reflux.**

**These statements are based upon homeopathic principles. They have not been reviewed by the Food and Drug Administration.

WARNINGS:

Keep out of reach of children. In case of overdose, contact a physician or Poison Control Center right away.

If pregnant or breast-feeding, ask a health professional before use.

Tamper seal: "Sealed for Your Protection." Do not use if seal is broken or missing.

Keep out of reach of children. In case of overdose, contact a physician or Poison Control Center right away.

DIRECTIONS:

1-10 drops under the tongue, 3 times a day or as directed by a health professional. Consult a physician for use in children under 12 years of age.

HOMEOPATHIC INDICATIONS:

For temporary relief of symptoms related to heartburn and esophageal reflux.**

**These statements are based upon homeopathic principles. They have not been reviewed by the Food and Drug Administration.

INACTIVE INGREDIENTS:

Demineralized Water, 25% Ethanol

QUESTIONS:

Dist. By: Deseret Biologicals, Inc.
469 W. Parkland Drive
Sandy, UT 84070 www.desbio.com

PACKAGE LABEL DISPLAY:

DESBIO

NDC 43742-1969-1

HOMEOPATHIC

REFL:HS

1 FL OZ (30 ml)